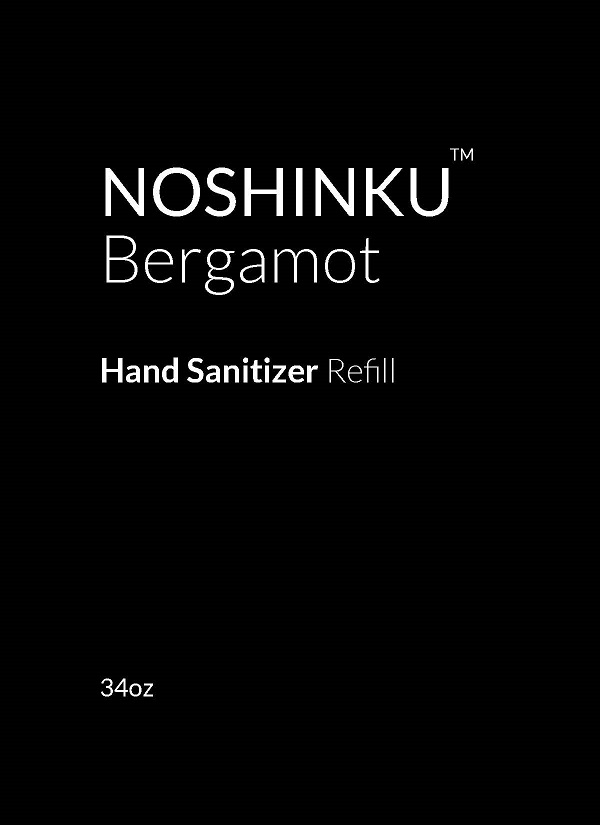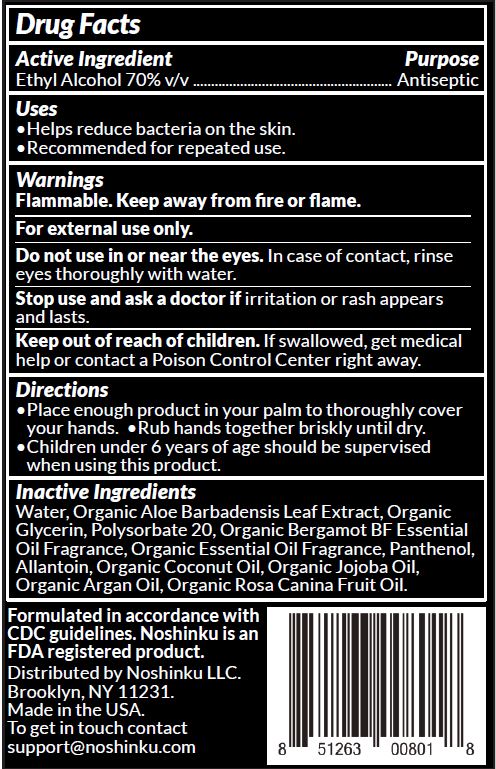 DRUG LABEL: Noshinku Bergamot Hand Sanitizer
NDC: 73898-001 | Form: SOLUTION
Manufacturer: Noshinku
Category: otc | Type: HUMAN OTC DRUG LABEL
Date: 20240514

ACTIVE INGREDIENTS: ALCOHOL 62.5 mL/100 mL
INACTIVE INGREDIENTS: ARGAN OIL; ALOE; ALLANTOIN; COCONUT OIL; JOJOBA OIL; ROSA CANINA FRUIT OIL; PANTHENOL; WATER; GLYCERIN; POLYSORBATE 20

Bergamot Hand Sanitizer (73898-001)

ACTIVE INGREDIENT

ETHYL ALCOHOL 62.5%

PURPOSE

ANTISEPTIC

USES

HELPS REDUCE BACTERIA ON THE SKIN. USE AS OFTEN AS NEEDED.

WARNINGS

FOR EXTERNAL USE ONLY.

FLAMMABLE. KEEP AWAY FROM FIRE OR FLAME.

STOP USE AND CONSULT A DOCTOR IF IRRITATION OR REDNESS DEVELOP. KEEP OUT OF EYES. IF CONTACT, RINSE EYES THOROUGHLY WITH WATER. DO NOT INGEST OR INHALE. AVOID USE ON BROKEN SKIN.

KEEP OUT OF REACH OF CHILDREN.

IF SWALLOWED, GET MEDICAL HELP OR CONTACT POISON CONTROL CENTER RIGHT AWAY.

DIRECTIONS

SPRAY LIQUID ONTO HANDS AND RUB UNTIL DRY.

INACTIVE INGREDIENTS

WATER, ORGANIC ALOE BARBADENSIS LEAF EXTRACT, ORGANIC SIMMONDSIA CHINENSIS (JOJOBA) OIL, ORGANIC VEGETABLE GLYCERIN, ORGANIC COCOS NUCIDERA (COCONUT) OIL, ORGANIC BERGAPTENE-FREE BERGAMIA OIL, ORGANIC CEDARWOOD OIL, ORGANIC ARGAN OIL, ORGANIC ROSEHIP SEED OIL, ORGANIC BLACK PEPPER OIL.